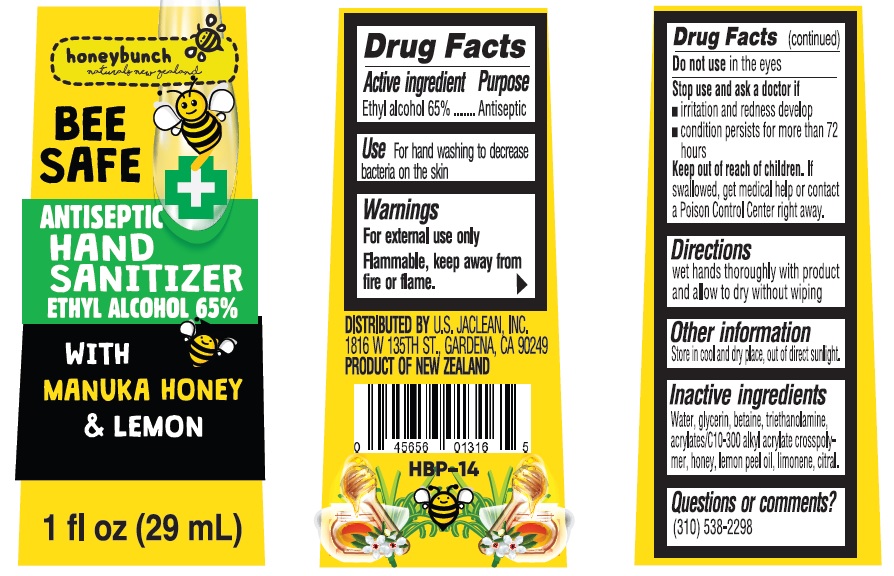 DRUG LABEL: Bee Safe Hand Sanitizer With Manuka Honey and Lemongrass
NDC: 78788-004 | Form: GEL
Manufacturer: HONEYBUNCH PURE NATURALS NZ LIMITED
Category: otc | Type: HUMAN OTC DRUG LABEL
Date: 20210714

ACTIVE INGREDIENTS: ALCOHOL 0.65 mL/1 mL
INACTIVE INGREDIENTS: WATER; GLYCERIN; BETAINE; TROLAMINE; MANUKA OIL; LEMON OIL; LIMONENE, (+)-; CITRAL

Bee Safe Hand Sanitizer With Manuka Honey and Lemongrass

Active Ingredient

Alcohol Denat. 65%

Purpose

Antiseptic

Use

Decrease Bacteria on hands

Warnings

Flammable. Keep away from flame or high heat.

For external use only.

When using this product

keep out of eyes.

Stop use and ask a doctor

if irritation or redness develops.

Keep out of reach of children.

If swallowed, get medical help or contact a Poison Control Center right away.

Directions:

Rub a dime sized drop into hands.

Inactive Ingredients

Water, Glycerin, Betaine, Triethanolamine, Acrylates/C10-300 Alkyl Acrylate Crosspolymer, Leptospermum Scoparium (Manuka) Mel, Citris Limon Peel Oil, Limonene, Citral.